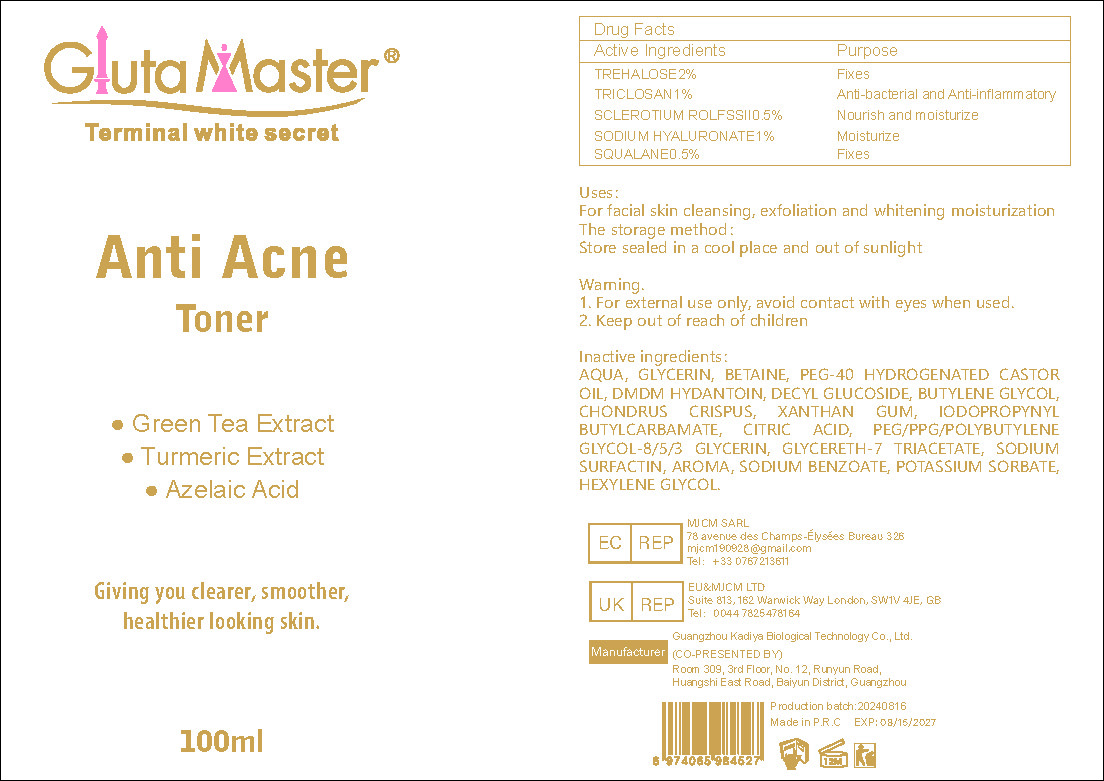 DRUG LABEL: Anti AcneToner
NDC: 84423-037 | Form: LOTION
Manufacturer: Guangzhou Kadiya Biotechnology Co., Ltd.
Category: otc | Type: HUMAN OTC DRUG LABEL
Date: 20240826

ACTIVE INGREDIENTS: SQUALANE 0.6 mg/100 mL; TRICLOSAN 1.2 mg/100 mL; TREHALOSE 2.4 mg/100 mL
INACTIVE INGREDIENTS: DECYL GLUCOSIDE; HEXYLENE GLYCOL; XANTHAN GUM; HYALURONATE SODIUM 1 mg/100 mL; GLYCERIN; CHONDRUS CRISPUS; GLYCERETH-7 TRIACETATE; SODIUM SURFACTIN; SODIUM BENZOATE; POLYOXYL 40 HYDROGENATED CASTOR OIL; DMDM HYDANTOIN; IODOPROPYNYL BUTYLCARBAMATE; POTASSIUM SORBATE; BETAINE; BUTYLENE GLYCOL; WATER; CITRIC ACID MONOHYDRATE

PURPOSE

For the improvement and lightening of redness on the face

INACTIVE INGREDIENT

AQUA、GLYCERIN、BETAINE、PEG-40 HYDROGENATED CASTOR OIL、DMDM HYDANTOIN、DECYL GLUCOSIDE、BUTYLENE GLYCOL、CHONDRUS CRISPUS、XANTHAN GUM、IODOPROPYNYL BUTYLCARBAMATE、CITRIC ACID、PEG/PPG/POLYBUTYLENE GLYCOL-8/5/3 GLYCERIN、GLYCERETH-7 TRIACETATE、SODIUM SURFACTIN、AROMA、SODIUM BENZOATE、POTASSIUM SORBATE、HEXYLENE GLYCOL

WARNINGS

1、For external use only, avoid contact with eyes when used
2、Keep out of reach of children

INDICATIONS AND USAGE

For facial skin cleansing, exfoliation and whitening moisturization

DOSAGE AND ADMINISTRATION

For facial skin cleansing, exfoliation and whitening moisturization

Active Ingredients
TREHALOSE2%
TRICLOSAN1%
SCLEROTIUM ROLFSSII0.5%
SODIUM HYALURONATE1%
SQUALANE0.5%

KEEP OUT OF REACH OF CHILDREN SECTION

PACKAGE LABEL

Active Ingredients
TREHALOSE2%
TRICLOSAN1%
SCLEROTIUM ROLFSSII0.5%
SODIUM HYALURONATE1%
SQUALANE0.5%

Uses：
For the improvement and lightening of redness on the face
The storage method：
Store sealed in a cool place and out of sunlight

Warning.
1、For external use only, avoid contact with eyes when used
2、Keep out of reach of children

Inactive ingredients：
AQUA、GLYCERIN、BETAINE、PEG-40 HYDROGENATED CASTOR OIL、DMDM HYDANTOIN、DECYL GLUCOSIDE、BUTYLENE GLYCOL、CHONDRUS CRISPUS、XANTHAN GUM、IODOPROPYNYL BUTYLCARBAMATE、CITRIC ACID、PEG/PPG/POLYBUTYLENE GLYCOL-8/5/3 GLYCERIN、GLYCERETH-7 TRIACETATE、SODIUM SURFACTIN、AROMA、SODIUM BENZOATE、POTASSIUM SORBATE、HEXYLENE GLYCOL